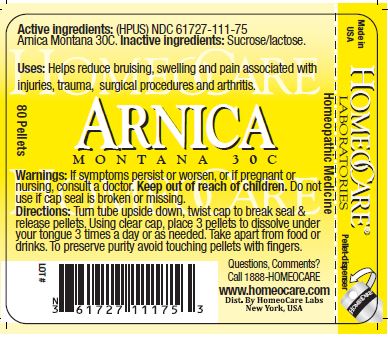 DRUG LABEL: Arnica Montana 30C
NDC: 61727-111 | Form: PELLET
Manufacturer: Homeocare Laboratories
Category: homeopathic | Type: HUMAN OTC DRUG LABEL
Date: 20190320

ACTIVE INGREDIENTS: ARNICA MONTANA 30 [hp_C]/1 1
INACTIVE INGREDIENTS: SUCROSE; LACTOSE

Arnica Montana 30C

Active Ingredients:

(HPUS) Arnica Montana 30C

Purpose:

Helps reduce bruising, swelling and pain associated with injuries, trauma, surgical procedures and arthritis.

Indications & Usage:

Helps reduce bruising, swelling, and pain associated with injuries, trauma, surgical procedures, and arthritis.

Warnings:

If symptoms persist or worsen, or if nursing, consult a doctor. Keep out of reach of children. Do not use if cap seal is broken or missing.

Keep out of reach of children.

Inactive Ingredients:

Sucrose/lactose.

Dosage & Administration:

Turn tube upside down, twist cap to break seal & release pellets. Using clear cap, place 3 pellets to dissolve under your tongue 3 times a day or as needed. Take apart from food or drinks. To preserve purity avoid touching pellets with fingers.